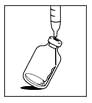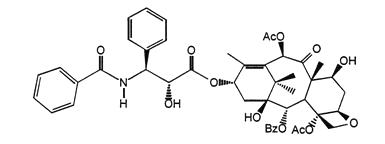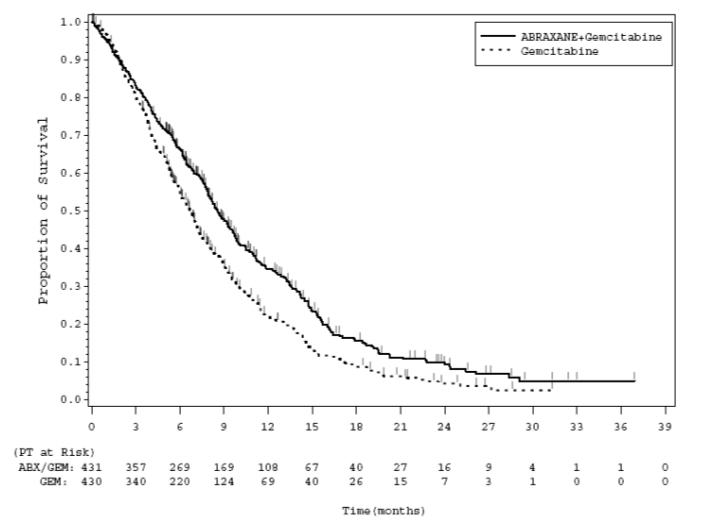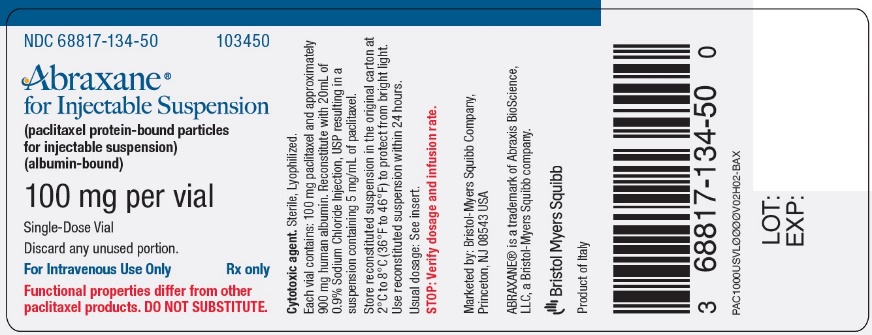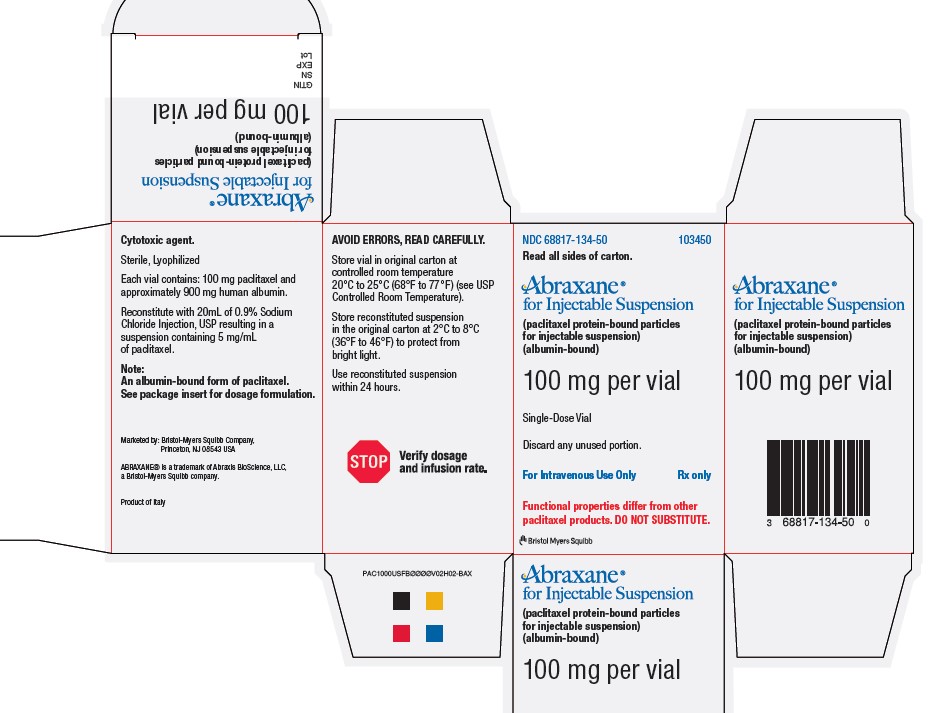 DRUG LABEL: ABRAXANE
NDC: 68817-134 | Form: INJECTION, POWDER, LYOPHILIZED, FOR SUSPENSION
Manufacturer: Abraxis BioScience, LLC
Category: prescription | Type: HUMAN PRESCRIPTION DRUG LABEL
Date: 20221031

ACTIVE INGREDIENTS: PACLITAXEL 100 mg/20 mL
INACTIVE INGREDIENTS: ALBUMIN HUMAN

HIGHLIGHTS OF PRESCRIBING INFORMATION

These highlights do not include all the information needed to use ABRAXANE safely and effectively. See full prescribing information for ABRAXANE.
ABRAXANE® for Injectable Suspension (paclitaxel protein-bound particles for injectable suspension)
(albumin-bound), for intravenous use
Initial U.S. Approval: 2005

WARNING: SEVERE MYELOSUPPRESSION

See full prescribing information for complete boxed warning.

- Do not administer ABRAXANE therapy to patients with baseline neutrophil counts of less than 1,500 cells/mm^3. (4)
- Monitor for neutropenia, which may be severe and result in infection or sepsis. (5.1, 5.3)
- Perform frequent complete blood cell counts on all patients receiving ABRAXANE. (5.1, 5.3)

RECENT MAJOR CHANGES

Dosage and Administration (2.1, 2.7) | 8/2020
Contraindications (4) | 8/2020
Warnings and Precautions (5.1, 5.2) | 8/2020

1 INDICATIONS AND USAGE

ABRAXANE is a microtubule inhibitor indicated for the treatment of:

- Metastatic breast cancer, after failure of combination chemotherapy for metastatic disease or relapse within 6 months of adjuvant chemotherapy. Prior therapy should have included an anthracycline unless clinically contraindicated. (1.1)
- Locally advanced or metastatic non-small cell lung cancer (NSCLC), as first-line treatment in combination with carboplatin, in patients who are not candidates for curative surgery or radiation therapy. (1.2)
- Metastatic adenocarcinoma of the pancreas as first-line treatment, in combination with gemcitabine. (1.3)

2 DOSAGE AND ADMINISTRATION

- Do not substitute ABRAXANE for other paclitaxel products. (2.1)
- Extravasation: Closely monitor the infusion site for extravasation and infiltration. (2.1)
- Metastatic Breast Cancer (MBC): Recommended dosage of ABRAXANE is 260 mg/m^2 intravenously over 30 minutes every 3 weeks. (2. 2)
- Non-Small Cell Lung Cancer (NSCLC): Recommended dosage of ABRAXANE is 100 mg/m^2 intravenously over 30 minutes on Days 1, 8, and 15 of each 21-day cycle; administer carboplatin on Day 1 of each 21-day cycle immediately after ABRAXANE. (2.3)
- Adenocarcinoma of the Pancreas: Recommended dosage of ABRAXANE is 125 mg/m^2 intravenously over 30-40 minutes on Days 1, 8, and 15 of each 28-day cycle; administer gemcitabine on Days 1, 8, and 15 of each 28-day cycle immediately after ABRAXANE. (2.4)
- Use in Patients with Hepatic Impairment: ABRAXANE is not recommended for use in patients with AST > 10 × ULN; or bilirubin > 5 × ULN or with metastatic adenocarcinoma of the pancreas who have moderate to severe hepatic impairment. For MBC or NSCLC, reduce starting dose in patients with moderate to severe hepatic impairment. (2.5)
- Dose Reductions for Adverse Reactions: Dose reductions or discontinuation may be needed based on severe hematologic, neurologic, cutaneous, or gastrointestinal toxicities. (2.6)

3 DOSAGE FORMS AND STRENGTHS

For injectable suspension: white to yellow, sterile, lyophilized powder containing 100 mg of paclitaxel formulated as albumin-bound particles in single-dose vial for reconstitution. (3)

4 CONTRAINDICATIONS

- Neutrophil counts of < 1,500 cells/mm^3. (4)
- Severe hypersensitivity reactions to ABRAXANE. (4)

5 WARNINGS AND PRECAUTIONS

- Sensory neuropathy occurs frequently and may require dose reduction or treatment interruption. (5.2)
- Sepsis occurred in patients with or without neutropenia who received ABRAXANE in combination with gemcitabine; interrupt ABRAXANE and gemcitabine until sepsis resolves, and if neutropenia, until neutrophils are at least 1500 cells/mm^3, then resume treatment at reduced dose levels. (5.3)
- Pneumonitis occurred with the use of ABRAXANE in combination with gemcitabine; permanently discontinue treatment with ABRAXANE and gemcitabine. (5.4)
- Severe hypersensitivity reactions with fatal outcome have been reported. Do not rechallenge with this drug. (4, 5.5)
- Exposure and toxicity of paclitaxel can be increased in patients with hepatic impairment, consider dose reduction and closely monitor patients with hepatic impairment. (2.5, 5.6)
- ABRAXANE contains albumin derived from human blood, which has a theoretical risk of viral transmission. (5.7)
- ABRAXANE can cause fetal harm. Advise patients of potential risk to a fetus and to use effective contraception. (5.8, 8.1, 8.3)

6 ADVERSE REACTIONS

- The most common adverse reactions (≥ 20%) in metastatic breast cancer are alopecia, neutropenia, sensory neuropathy, abnormal ECG, fatigue/asthenia, myalgia/arthralgia, AST elevation, alkaline phosphatase elevation, anemia, nausea, infections, and diarrhea. (6.1)
- The most common adverse reactions (≥ 20%) in NSCLC are anemia, neutropenia, thrombocytopenia, alopecia, peripheral neuropathy, nausea, and fatigue. (6.1)
- The most common (≥ 20%) adverse reactions of ABRAXANE in adenocarcinoma of the pancreas are neutropenia, fatigue, peripheral neuropathy, nausea, alopecia, peripheral edema, diarrhea, pyrexia, vomiting, decreased appetite, rash, and dehydration. (6.1)

To report SUSPECTED ADVERSE REACTIONS, contact Bristol-Myers Squibb at 1-800-721-5072 or FDA at 1-800-FDA-1088 or www.fda.gov/medwatch.

7 DRUG INTERACTIONS

Use caution when concomitantly administering ABRAXANE with inhibitors or inducers of either CYP2C8 or CYP3A4. (7)

8 USE IN SPECIFIC POPULATIONS

- Lactation: Advise not to breastfeed. (8.2)

FULL PRESCRIBING INFORMATION

ABRAXANE® for Injectable Suspension (paclitaxel protein-bound particles for injectable suspension) (albumin-bound)

WARNING: SEVERE MYELOSUPPRESSION

- Do not administer ABRAXANE therapy to patients with baseline neutrophil counts of less than 1,500 cells/mm^3 [see Contraindications (4)].
- Monitor for neutropenia, which may be severe and result in infection or sepsis [see Warnings and Precautions (5.1, 5.3)].
- Perform frequent complete blood cell counts on all patients receiving ABRAXANE [see Warnings and Precautions (5.1, 5.3)].

1 INDICATIONS AND USAGE

1.1 Metastatic Breast Cancer

ABRAXANE is indicated for the treatment of breast cancer after failure of combination chemotherapy for metastatic disease or relapse within 6 months of adjuvant chemotherapy. Prior therapy should have included an anthracycline unless clinically contraindicated.

1.2 Non-Small Cell Lung Cancer

ABRAXANE is indicated for the first-line treatment of locally advanced or metastatic non-small cell lung cancer, in combination with carboplatin, in patients who are not candidates for curative surgery or radiation therapy.

1.3 Adenocarcinoma of the Pancreas

ABRAXANE is indicated for the first-line treatment of patients with metastatic adenocarcinoma of the pancreas, in combination with gemcitabine.

2 DOSAGE AND ADMINISTRATION

2.1 Important Administration Instructions

DO NOT SUBSTITUTE FOR OR WITH OTHER PACLITAXEL FORMULATIONS. ABRAXANE has different dosage and administration instructions from other paclitaxel products.

Closely monitor the infusion site for extravasation or drug infiltration during administration. Limiting the infusion of ABRAXANE to 30 minutes may reduce the risk of infusion-related reactions [see Adverse Reactions (6.2)].

Consider premedication in patients who have had prior hypersensitivity reactions to ABRAXANE. Do not re-challenge patients who experience a severe hypersensitivity reaction to ABRAXANE [see Contraindications (4) and Warnings and Precautions (5.5)].

2.2 Recommended Dosage for Metastatic Breast Cancer

After failure of combination chemotherapy for metastatic breast cancer or relapse within 6 months of adjuvant chemotherapy, the recommended regimen for ABRAXANE is 260 mg/m^2 administered intravenously over 30 minutes every 3 weeks.

2.3 Recommended Dosage for Non-Small Cell Lung Cancer

The recommended dose of ABRAXANE is 100 mg/m^2 administered as an intravenous infusion over 30 minutes on Days 1, 8, and 15 of each 21-day cycle. Administer carboplatin on Day 1 of each 21-day cycle immediately after ABRAXANE [see Clinical Studies (14.2)].

2.4 Recommended Dosage for Adenocarcinoma of the Pancreas

The recommended dose of ABRAXANE is 125 mg/m^2 administered as an intravenous infusion over 30-40 minutes on Days 1, 8, and 15 of each 28-day cycle. Administer gemcitabine immediately after ABRAXANE on Days 1, 8, and 15 of each 28-day cycle [see Clinical Studies (14.3)].

2.5 Dosage Modifications for Hepatic Impairment

For patients with moderate or severe hepatic impairment, reduce the starting dose of ABRAXANE as shown in Table 1.

Table 1: Recommendations for Starting Dose in Patients with Moderate and Severe Hepatic Impairment
 | AST Levels |  | Bilirubin Levels | ABRAXANE Dosea
 | AST Levels |  | Bilirubin Levels | MBC | NSCLC c | Adenocarcinoma of Pancreasc
Moderate | < 10 x ULN | AND | > 1.5 to ≤ 3 x ULN | 200 mg/m2 b | 80 mg/m2 b | not recommended
Severe | < 10 x ULN | AND | > 3 to ≤ 5 x ULN | 200 mg/m2 b | 80 mg/m2 b | not recommended
 | > 10 x ULN | OR | > 5 x ULN | not recommended | not recommended | not recommended
AST = Aspartate Aminotransferase; MBC = Metastatic Breast Cancer; NSCLC = Non-Small Cell Lung Cancer; ULN = Upper limit of normal.
a Dosage recommendations are for the first course of therapy. The need for further dose adjustments in subsequent courses should be based on individual tolerance.
b A dose increase to 260 mg/m^2 for patients with metastatic breast cancer or 100 mg/m^2 for patients with non-small cell lung cancer in subsequent courses should be considered if the patient tolerates the reduced dose for two cycles.
c Patients with bilirubin levels above the upper limit of normal were excluded from clinical trials for pancreatic or lung cancer.

2.6 Dosage Modifications for Adverse Reactions

Metastatic Breast Cancer
Patients who experience severe neutropenia (neutrophils less than 500 cells/mm^3 for a week or longer) or severe sensory neuropathy during ABRAXANE therapy should have dosage reduced to 220 mg/m^2 for subsequent courses of ABRAXANE. For recurrence of severe neutropenia or severe sensory neuropathy, additional dose reduction should be made to 180 mg/m^2. For Grade 3 sensory neuropathy hold treatment until resolution to Grade 1 or 2, followed by a dose reduction for all subsequent courses of ABRAXANE [see Contraindications (4), Warnings and Precautions (5.1, 5.2) and Adverse Reactions (6.1)].

Non-Small Cell Lung Cancer

- Do not administer ABRAXANE on Day 1 of a cycle until absolute neutrophil count (ANC) is at least 1500 cells/mm^3 and platelet count is at least 100,000 cells/mm^3 [see Contraindications (4), Warnings and Precautions (5.1) and Adverse Reactions (6.1)].
- In patients who develop severe neutropenia or thrombocytopenia withhold treatment until counts recover to an absolute neutrophil count of at least 1500 cells/mm^3 and platelet count of at least 100,000 cells/mm^3 on Day 1 or to an absolute neutrophil count of at least 500 cells/mm^3 and platelet count of at least 50,000 cells/mm^3 on Days 8 or 15 of the cycle. Upon resumption of dosing, permanently reduce ABRAXANE and carboplatin doses as outlined in Table 2.
- Withhold ABRAXANE for Grade 3-4 peripheral neuropathy. Resume ABRAXANE and carboplatin at reduced doses (see Table 2) when peripheral neuropathy improves to Grade 1 or completely resolves [see Warnings and Precautions (5.2) and Adverse Reactions (6.1)].

Table 2: Permanent Dose Reductions for Hematologic and Neurologic Adverse Reactions in NSCLC
Adverse Reaction | Occurrence | Weekly ABRAXANE Dose (mg/m^2) | Every 3-Week Carboplatin Dose (AUC mg•min/mL)
Neutropenic Fever (ANC less than 500/mm^3 with fever >38°C) OR Delay of next cycle by more than 7 days for ANC less than 1500/mm^3 OR ANC less than 500/mm^3 for more than 7 days | First | 75 | 4.5
Neutropenic Fever (ANC less than 500/mm^3 with fever >38°C) OR Delay of next cycle by more than 7 days for ANC less than 1500/mm^3 OR ANC less than 500/mm^3 for more than 7 days | Second | 50 | 3
Neutropenic Fever (ANC less than 500/mm^3 with fever >38°C) OR Delay of next cycle by more than 7 days for ANC less than 1500/mm^3 OR ANC less than 500/mm^3 for more than 7 days | Third | Discontinue Treatment
Platelet count less than 50,000/mm^3 | First | 75 | 4.5
Platelet count less than 50,000/mm^3 | Second | Discontinue Treatment
Severe sensory Neuropathy – Grade 3 or 4 | First | 75 | 4.5
Severe sensory Neuropathy – Grade 3 or 4 | Second | 50 | 3
Severe sensory Neuropathy – Grade 3 or 4 | Third | Discontinue Treatment

Adenocarcinoma of the Pancreas
Dose level reductions for patients with adenocarcinoma of the pancreas, as referenced in Tables 4 and 5, are provided in Table 3.

Table 3: Dose Level Reductions for Patients with Adenocarcinoma of the Pancreas
Dose Level | ABRAXANE (mg/m^2) | Gemcitabine (mg/m^2)
Full dose | 125 | 1000
1st dose reduction | 100 | 800
2nd dose reduction | 75 | 600
If additional dose reduction required | Discontinue | Discontinue

Recommended dose modifications for neutropenia and thrombocytopenia for patients with adenocarcinoma of the pancreas are provided in Table 4.

Table 4: Dose Recommendation and Modifications for Neutropenia and/or Thrombocytopenia at the Start of a Cycle or within a Cycle for Patients with Adenocarcinoma of the Pancreas
Cycle Day | ANC (cells/mm^3) |  | Platelet count (cells/mm^3) | ABRAXANE / Gemcitabine
Day 1 | < 1500 | OR | < 100,000 | Delay doses until recovery
Day 8 | 500 to < 1000 | OR | 50,000 to < 75,000 | Reduce 1 dose level
 | < 500 | OR | < 50,000 | Withhold doses
Day 15: If Day 8 doses were reduced or given without modification:
 | 500 to < 1000 | OR | 50,000 to < 75,000 | Reduce 1 dose level from Day 8
 | < 500 | OR | < 50,000 | Withhold doses
Day 15: If Day 8 doses were withheld:
 | ≥ 1000 | OR | ≥ 75,000 | Reduce 1 dose level from Day 1
 | 500 to < 1000 | OR | 50,000 to < 75,000 | Reduce 2 dose levels from Day 1
 | < 500 | OR | < 50,000 | Withhold doses
ANC = Absolute Neutrophil Count

Recommended dose modifications for other adverse reactions in patients with adenocarcinoma of the pancreas are provided in Table 5.

Table 5: Dose Modifications for Other Adverse Reactions in Patients with Adenocarcinoma of the Pancreas
Adverse Reaction | ABRAXANE | Gemcitabine
Febrile Neutropenia: Grade 3 or 4 | Withhold until fever resolves and ANC ≥ 1500; resume at next lower dose level
Peripheral Neuropathy: Grade 3 or 4 | Withhold until improves to ≤ Grade 1; resume at next lower dose level | No dose reduction
Cutaneous Toxicity: Grade 2 or 3 | Reduce to next lower dose level; discontinue treatment if toxicity persists
Gastrointestinal Toxicity: Grade 3 mucositis or diarrhea | Withhold until improves to ≤ Grade 1; resume at next lower dose level

2.7 Preparation for Intravenous Administration

ABRAXANE is a cytotoxic drug. Follow applicable special handling and disposal procedures.^1 The use of gloves is recommended. If ABRAXANE (lyophilized cake or reconstituted suspension) contacts the skin, wash the skin immediately and thoroughly with soap and water. Following topical exposure to paclitaxel, events may include tingling, burning, and redness. If ABRAXANE contacts mucous membranes, the membranes should be flushed thoroughly with water.

ABRAXANE is supplied as a sterile lyophilized powder for reconstitution before use.

Read the entire preparation instructions prior to reconstitution.

1. Aseptically, reconstitute each vial by injecting 20 mL of 0.9% Sodium Chloride Injection, USP.
2. Slowly inject the 20 mL of 0.9% Sodium Chloride Injection, USP, over a minimum of 1 minute, using the
  sterile syringe to direct the solution flow onto the INSIDE WALL OF THE VIAL.
3. DO NOT INJECT the 0.9% Sodium Chloride Injection, USP, directly onto the lyophilized cake as this
  will result in foaming.
4. Once the injection is complete, allow the vial to sit for a minimum of 5 minutes to ensure proper wetting of
  the lyophilized cake/powder.
5. Gently swirl and/or invert the vial slowly for at least 2 minutes until complete dissolution of any cake/powder
  occurs. Avoid generation of foam.
6. If foaming or clumping occurs, stand solution for at least 15 minutes until foam subsides.

Each mL of the reconstituted formulation will contain 5 mg/mL paclitaxel.

The reconstituted suspension should be milky and homogenous without visible particulates. If particulates or settling are visible, the vial should be gently inverted again to ensure complete resuspension prior to use. Discard the reconstituted suspension if precipitates are observed. Discard any unused portion.

Calculate the exact total dosing volume of 5 mg/mL suspension required for the patient and slowly withdraw the dosing volume of the reconstituted suspension from the vial(s) into a syringe: Dosing volume (mL)=Total dose (mg)/5 (mg/mL).

Inject the appropriate amount of reconstituted ABRAXANE into an empty, sterile intravenous bag [plasticized polyvinyl chloride (PVC) containers, PVC or non-PVC type intravenous bag]. The use of specialized DEHP-free solution containers or administration sets is not necessary to prepare or administer ABRAXANE infusions. The use of medical devices containing silicone oil as a lubricant (i.e., syringes and intravenous bags) to reconstitute and administer ABRAXANE may result in the formation of proteinaceous strands.

Visually inspect the reconstituted ABRAXANE suspension in the intravenous bag prior to administration. Discard the reconstituted suspension if proteinaceous strands, particulate matter, or discoloration are observed.

2.8 Stability

Unopened vials of ABRAXANE are stable until the date indicated on the package when stored between 20°C to 25°C (68°F to 77°F) in the original package. Neither freezing nor refrigeration adversely affects the stability of the product.

Stability of Reconstituted Suspension in the Vial
Reconstituted ABRAXANE in the vial should be used immediately, but may be refrigerated at 2°C to 8°C (36°F to 46°F) for a maximum of 24 hours if necessary. If not used immediately, each vial of reconstituted suspension should be replaced in the original carton to protect it from bright light. Discard any unused portion.

Stability of Reconstituted Suspension in the Infusion Bag
The suspension for infusion when prepared as recommended in an infusion bag should be used immediately, but may be refrigerated at 2°C to 8°C (36°F to 46°F) and protected from bright light for a maximum of 24 hours.

The total combined refrigerated storage time of reconstituted ABRAXANE in the vial and in the infusion bag is 24 hours. This may be followed by storage in the infusion bag at ambient temperature (approximately 25°C) and lighting conditions for a maximum of 4 hours.

Discard any unused portion.

3 DOSAGE FORMS AND STRENGTHS

For injectable suspension, for intravenous use: white to yellow, sterile lyophilized powder containing 100 mg of paclitaxel formulated as albumin-bound particles in single-dose vial for reconstitution.

4 CONTRAINDICATIONS

ABRAXANE is contraindicated in patients with:

- Baseline neutrophil counts of < 1,500 cells/mm^3 [see Warnings and Precautions (5.1)]
- A history of severe hypersensitivity reactions to ABRAXANE [see Warnings and Precautions (5.5)]

5 WARNINGS AND PRECAUTIONS

5.1 Severe Myelosuppression

Severe myelosuppression (primarily neutropenia) is dose-dependent and a dose-limiting toxicity of ABRAXANE. In clinical studies, Grade 3-4 neutropenia occurred in 34% of patients with metastatic breast cancer (MBC), 47% of patients with non-small cell lung cancer (NSCLC), and 38% of patients with pancreatic cancer.

Monitor for severe neutropenia and thrombocytopenia by performing complete blood cell counts frequently, including prior to dosing on Day 1 (for MBC) and Days 1, 8, and 15 (for NSCLC and for pancreatic cancer). Do not administer ABRAXANE to patients with baseline absolute neutrophil counts (ANC) of less than 1,500 cells/mm3 [see Contraindications (4)].

In the case of severe neutropenia (<500 cells/mm^3 for seven days or more) during a course of ABRAXANE therapy, reduce the dose of ABRAXANE in subsequent courses in patients with either MBC or NSCLC.

In patients with MBC, resume treatment with every-3-week cycles of ABRAXANE after ANC recovers to a level >1,500 cells/mm^3 and platelets recover to a level >100,000 cells/mm^3. In patients with NSCLC, resume treatment if recommended at permanently reduced doses for both weekly ABRAXANE and every-3-week carboplatin after ANC recovers to at least 1500 cells/mm^3 and platelet count of at least 100,000 cells/mm^3 on Day 1 or to an ANC of at least 500 cells/mm^3 and platelet count of at least 50,000 cells/mm^3 on Days 8 or 15 of the cycle [see Dosage and Administration (2.6)].

In patients with adenocarcinoma of the pancreas, withhold ABRAXANE and gemcitabine if the ANC is less than 500 cells/mm^3 or platelets are less than 50,000 cells/mm^3 and delay initiation of the next cycle if the ANC is less than 1500 cells/mm^3 or platelet count is less than 100,000 cells/mm^3 on Day 1 of the cycle. Resume treatment with appropriate dose reduction if recommended [see Dosage and Administration (2.6)].

5.2 Severe Neuropathy

Sensory neuropathy is dose- and schedule-dependent [see Adverse Reactions (6.1)]. If ≥ Grade 3 sensory neuropathy develops, withhold ABRAXANE treatment until resolution to Grade 1 or 2 for metastatic breast cancer or until resolution to ≤ Grade 1 for NSCLC and pancreatic cancer followed by a dose reduction for all subsequent courses of ABRAXANE [see Dosage and Administration (2.6)].

5.3 Sepsis

Sepsis occurred in 5% of patients with or without neutropenia who received ABRAXANE in combination with gemcitabine. Biliary obstruction or presence of biliary stent were risk factors for severe or fatal sepsis. If a patient becomes febrile (regardless of ANC) initiate treatment with broad spectrum antibiotics. For febrile neutropenia, interrupt ABRAXANE and gemcitabine until fever resolves and ANC ≥ 1500, then resume treatment at reduced dose levels [see Dosage and Administration (2.6)].

5.4 Pneumonitis

Pneumonitis, including some cases that were fatal, occurred in 4% of patients receiving ABRAXANE in combination with gemcitabine.

Monitor patients for signs and symptoms of pneumonitis and interrupt ABRAXANE and gemcitabine during evaluation of suspected pneumonitis. After ruling out infectious etiology and upon making a diagnosis of pneumonitis, permanently discontinue treatment with ABRAXANE and gemcitabine.

5.5 Severe Hypersensitivity

Severe and sometimes fatal hypersensitivity reactions, including anaphylactic reactions, have been reported. Do not rechallenge patients who experience a severe hypersensitivity reaction to ABRAXANE with this drug [see Contraindications (4)].

Cross-hypersensitivity between ABRAXANE and other taxane products has been reported and may include severe reactions such as anaphylaxis. Closely monitor patients with a previous history of hypersensitivity to other taxanes during initiation of ABRAXANE therapy.

5.6 Use in Patients with Hepatic Impairment

The exposure and toxicity of paclitaxel can be increased in patients with hepatic impairment. Closely monitor patients with hepatic impairment for severe myelosuppression.

ABRAXANE is not recommended in patients who have total bilirubin >5 x ULN or AST >10 x ULN. In addition, ABRAXANE is not recommended in patients with metastatic adenocarcinoma of the pancreas who have moderate to severe hepatic impairment (total bilirubin >1.5 x ULN and AST ≤10 x ULN). Reduce the starting dose for patients with moderate or severe hepatic impairment [see Dosage and Administration (2.5), Use in Specific Populations (8.7), Clinical Pharmacology (12.3)].

5.7 Albumin (Human)

ABRAXANE contains albumin (human), a derivative of human blood. Based on effective donor screening and product manufacturing processes, it carries a remote risk for transmission of viral diseases. A theoretical risk for transmission of Creutzfeldt-Jakob Disease (CJD) also is considered extremely remote. No cases of transmission of viral diseases or CJD have ever been identified for albumin.

5.8 Embryo-Fetal Toxicity

Based on mechanism of action and findings in animals, ABRAXANE can cause fetal harm when administered to a pregnant woman. In animal reproduction studies, administration of paclitaxel formulated as albumin-bound particles to rats during pregnancy at doses lower than the maximum recommended human dose, based on body surface area, caused embryo-fetal toxicities, including intrauterine mortality, increased resorptions, reduced numbers of live fetuses, and malformations.

Advise females of reproductive potential of the potential risk to a fetus. Advise females of reproductive potential to use effective contraception and avoid becoming pregnant during treatment with ABRAXANE and for at least six months after the last dose of ABRAXANE [see Use in Specific Populations (8.1, 8.3), Clinical Pharmacology (12.1)].

Based on findings from genetic toxicity and animal reproduction studies, advise male patients with female partners of reproductive potential to use effective contraception and avoid fathering a child during treatment with ABRAXANE and for at least three months after the last dose of ABRAXANE [see Use in Specific Populations (8.1, 8.3), Nonclinical Toxicology (13.1)].

6 ADVERSE REACTIONS

Because clinical trials are conducted under widely varying conditions, adverse reaction rates observed in the clinical trials of a drug cannot be directly compared to rates in the clinical trials of another drug and may not reflect the rates observed in practice.

The most common adverse reactions (≥ 20%) with single-agent use of ABRAXANE in metastatic breast cancer are alopecia, neutropenia, sensory neuropathy, abnormal ECG, fatigue/asthenia, myalgia/arthralgia, AST elevation, alkaline phosphatase elevation, anemia, nausea, infections, and diarrhea [see Adverse Reactions (6.1)].

The most common adverse reactions (≥ 20%) of ABRAXANE in combination with carboplatin for non-small cell lung cancer are anemia, neutropenia, thrombocytopenia, alopecia, peripheral neuropathy, nausea, and fatigue [see Adverse Reactions (6.1)]. The most common serious adverse reactions of ABRAXANE in combination with carboplatin for non-small cell lung cancer are anemia (4%) and pneumonia (3%). The most common adverse reactions resulting in permanent discontinuation of ABRAXANE are neutropenia (3%), thrombocytopenia (3%), and peripheral neuropathy (1%). The most common adverse reactions resulting in dose reduction of ABRAXANE are neutropenia (24%), thrombocytopenia (13%), and anemia (6%). The most common adverse reactions leading to withholding or delay in ABRAXANE dosing are neutropenia (41%), thrombocytopenia (30%), and anemia (16%).

In a randomized open-label trial of ABRAXANE in combination with gemcitabine for pancreatic adenocarcinoma [see Clinical Studies (14.3)], the most common (≥ 20%) selected (with a ≥ 5% higher incidence) adverse reactions of ABRAXANE are neutropenia, fatigue, peripheral neuropathy, nausea, alopecia, peripheral edema, diarrhea, pyrexia, vomiting, decreased appetite, rash, and dehydration [see Adverse Reactions (6.1)]. The most common serious adverse reactions of ABRAXANE (with a ≥ 1% higher incidence) are pyrexia (6%), dehydration (5%), pneumonia (4%), and vomiting (4%). The most common adverse reactions resulting in permanent discontinuation of ABRAXANE are peripheral neuropathy (8%), fatigue (4%), and thrombocytopenia (2%). The most common adverse reactions resulting in dose reduction of ABRAXANE are neutropenia (10%) and peripheral neuropathy (6%). The most common adverse reactions leading to withholding or delay in ABRAXANE dosing are neutropenia (16%), thrombocytopenia (12%), fatigue (8%), peripheral neuropathy (15%), anemia (5%), and diarrhea (5%).

6.1 Clinical Trials Experience

Metastatic Breast Cancer

Table 6 shows the frequency of important adverse reactions in the randomized comparative trial for the patients who received either single-agent ABRAXANE or paclitaxel injection for the treatment of metastatic breast cancer.

Table 6: Adverse Reactions in the Randomized Metastatic Breast Cancer Study on an Every-3-Weeks Schedule
 | Percent of Patients
 | ABRAXANE 260 mg/m^2 over 30 min (n=229) | Paclitaxel Injection 175 mg/m^2 over 3 ha (n=225)
Bone Marrow
Neutropenia
< 2.0 x 10^9/L | 80 | 82
< 0.5 x 10^9/L | 9 | 22
Thrombocytopenia
< 100 x 10^9/L | 2 | 3
< 50 x 10^9/L | <1 | <1
Anemia
< 11 g/dL | 33 | 25
< 8 g/dL | 1 | <1
Infections | 24 | 20
Febrile Neutropenia | 2 | 1
Neutropenic Sepsis | <1 | <1
Bleeding | 2 | 2
Hypersensitivity Reactionb
All | 4 | 12
Severec | 0 | 2
Cardiovascular
Vital Sign Changes During Administration
Bradycardia | <1 | <1
Hypotension | 5 | 5
Severe Cardiovascular Eventsc | 3 | 4
Abnormal ECG
All Patients | 60 | 52
Patients with Normal Baseline | 35 | 30
Respiratory
Cough | 7 | 6
Dyspnea | 12 | 9
Sensory Neuropathy
Any Symptoms | 71 | 56
Severe Symptomsc | 10 | 2
Myalgia / Arthralgia
Any Symptoms | 44 | 49
Severe Symptomsc | 8 | 4
Asthenia
Any Symptoms | 47 | 39
Severe Symptomsc | 8 | 3
Fluid Retention/Edema
Any Symptoms | 10 | 8
Severe Symptomsc | 0 | <1
Gastrointestinal
Nausea
Any Symptoms | 30 | 22
Severe Symptomsc | 3 | <1
Vomiting
Any Symptoms | 18 | 10
Severe Symptomsc | 4 | 1
Diarrhea
Any Symptoms | 27 | 15
Severe Symptomsc | <1 | 1
Mucositis
Any Symptoms | 7 | 6
Severe Symptomsc | <1 | 0
Alopecia | 90 | 94
Hepatic (Patients with Normal Baseline)
Bilirubin Elevations | 7 | 7
Alkaline Phosphatase Elevations | 36 | 31
AST (SGOT) Elevations | 39 | 32
Injection Site Reaction | <1 | 1
a Paclitaxel injection patients received premedication.
b Includes treatment-related events related to hypersensitivity (e.g., flushing, dyspnea, chest pain, hypotension) that began on a day of dosing.
c Severe events are defined as at least Grade 3 toxicity.

Other Adverse Reactions

Hematologic Disorders
Neutropenia was dose dependent and reversible. Among patients with metastatic breast cancer in the randomized trial, neutrophil counts declined below 500 cells/mm^3 (Grade 4) in 9% of the patients treated with a dose of 260 mg/m^2 compared to 22% in patients receiving paclitaxel injection at a dose of 175 mg/m^2. Pancytopenia has been observed in clinical trials.

Infections
Infectious episodes were reported in 24% of the patients treated with ABRAXANE. Oral candidiasis, respiratory tract infections and pneumonia were the most frequently reported infectious complications.

Hypersensitivity Reactions (HSRs)
Grade 1 or 2 HSRs occurred on the day of ABRAXANE administration and consisted of dyspnea (1%) and flushing, hypotension, chest pain, and arrhythmia (all <1%). The use of ABRAXANE in patients previously exhibiting hypersensitivity to paclitaxel injection or human albumin has not been studied.

Cardiovascular
Hypotension, during the 30-minute infusion, occurred in 5% of patients. Bradycardia, during the 30-minute infusion, occurred in <1% of patients. These vital sign changes most often caused no symptoms and required neither specific therapy nor treatment discontinuation.

Severe cardiovascular events possibly related to single-agent ABRAXANE occurred in approximately 3% of patients. These events included cardiac ischemia/infarction, chest pain, cardiac arrest, supraventricular tachycardia, edema, thrombosis, pulmonary thromboembolism, pulmonary emboli, and hypertension. Cases of cerebrovascular attacks (strokes) and transient ischemic attacks have been reported.

Electrocardiogram (ECG) abnormalities were common among patients at baseline. ECG abnormalities on study did not usually result in symptoms, were not dose-limiting, and required no intervention. ECG abnormalities were noted in 60% of patients. Among patients with a normal ECG prior to study entry, 35% of all patients developed an abnormal tracing while on study. The most frequently reported ECG modifications were non-specific repolarization abnormalities, sinus bradycardia, and sinus tachycardia.

Respiratory
Dyspnea (12%), cough (7%), and pneumothorax (<1%) were reported after treatment with ABRAXANE.

Neurologic
The frequency and severity of sensory neuropathy increased with cumulative dose. Sensory neuropathy was the cause of ABRAXANE discontinuation in 7/229 (3%) patients. Twenty-four patients (10%) treated with ABRAXANE developed Grade 3 peripheral neuropathy; of these patients, 14 had documented improvement after a median of 22 days; 10 patients resumed treatment at a reduced dose of ABRAXANE and 2 discontinued due to peripheral neuropathy. Of the 10 patients without documented improvement, 4 discontinued the study due to peripheral neuropathy.

No Grade 4 sensory neuropathies were reported. Only one incident of motor neuropathy (Grade 2) was observed in either arm of the controlled trial.

Vision Disorders
Ocular/visual disturbances occurred in 13% of all patients (n=366) treated with ABRAXANE and 1% were severe. The severe cases (keratitis and blurred vision) were reported in patients who received higher doses than those recommended (300 or 375 mg/m^2). These effects generally have been reversible.

Arthralgia/Myalgia
The symptoms were usually transient, occurred two or three days after ABRAXANE administration, and resolved within a few days.

Hepatic
Grade 3 or 4 elevations in GGT were reported for 14% of patients treated with ABRAXANE and 10% of patients treated with paclitaxel injection in the randomized trial.

Renal
Overall 11% of patients experienced creatinine elevation, 1% severe. No discontinuations, dose reductions, or dose delays were caused by renal toxicities.

Other Clinical Events
Nail changes (changes in pigmentation or discoloration of nail bed) have been reported. Edema occurred in 10% of patients; no patients had severe edema. Dehydration and pyrexia were also reported.

Non-Small Cell Lung Cancer

Adverse reactions were assessed in 514 ABRAXANE/carboplatin-treated patients and 524 paclitaxel injection/carboplatin-treated patients receiving first-line systemic treatment for locally advanced (stage IIIB) or metastatic (IV) non-small cell lung cancer (NSCLC) in a multicenter, randomized, open-label trial. ABRAXANE was administered as an intravenous infusion over 30 minutes at a dose of 100 mg/m^2 on Days 1, 8, and 15 of each 21-day cycle. Paclitaxel injection was administered as an intravenous infusion over 3 hours at a dose of 200 mg/m^2, following premedication. In both treatment arms carboplatin at a dose of AUC = 6 mg•min/mL was administered intravenously on Day 1 of each 21-day cycle after completion of ABRAXANE/paclitaxel infusion.

The differences in paclitaxel dose and schedule between the two arms limit direct comparison of dose- and schedule-dependent adverse reactions. Among patients evaluable for adverse reactions, the median age was 60 years, 75% were men, 81% were White, 49% had adenocarcinoma, 43% had squamous cell lung cancer, 76% were ECOG PS 1. Patients in both treatment arms received a median of 6 cycles of treatment.

The following common (≥ 10% incidence) adverse reactions were observed at a similar incidence in ABRAXANE plus carboplatin-treated and paclitaxel injection plus carboplatin-treated patients: alopecia 56%, nausea 27%, fatigue 25%, decreased appetite 17%, asthenia 16%, constipation 16%, diarrhea 15%, vomiting 12%, dyspnea 12%, and rash 10% (incidence rates are for the ABRAXANE plus carboplatin treatment group).

Table 7 provides the frequency and severity of laboratory-detected abnormalities which occurred with a difference of ≥ 5% for all grades (1-4) or ≥ 2% for Grade 3-4 toxicity between ABRAXANE plus carboplatin-treated patients or paclitaxel injection plus carboplatin-treated patients.

Table 7: Selected Hematologic Laboratory-Detected Abnormalities with a Difference of ≥ 5% for grades (1-4) or ≥ 2% for Grade 3-4 Toxicity Between Treatment Groups
 | ABRAXANE (100 mg/m^2 weekly) plus carboplatin |  | Paclitaxel Injection (200 mg/m^2 every 3 weeks) plus carboplatin
 | Grades 1-4 (%) | Grade 3-4 (%) | Grades 1-4 (%) | Grade 3-4 (%)
Anemia^1,2 | 98 | 28 | 91 | 7
Neutropenia^1,3 | 85 | 47 | 83 | 58
Thrombocytopenia^1,3 | 68 | 18 | 55 | 9
^1 508 patients assessed in ABRAXANE/carboplatin-treated group.
^2 514 patients assessed in paclitaxel injection/carboplatin-treated group.
^3 513 patients assessed in paclitaxel injection/carboplatin-treated group.

Table 8 provides the frequency and severity of adverse reactions, which occurred with a difference of ≥ 5% for all grades (1-4) or ≥ 2% for Grade 3-4 between either treatment group for the 514 ABRAXANE plus carboplatin-treated patients compared with the 524 patients who received paclitaxel injection plus carboplatin.

Table 8: Selected Adverse Reactions with a Difference of ≥5% for All Grade Toxicity or ≥2% for Grade 3-4 Toxicity Between Treatment Groups
System Organ Class | Adverse Reaction | ABRAXANE (100 mg/m^2 weekly) + carboplatin (N=514) |  | Paclitaxel Injection (200 mg/m^2 every 3 weeks) + carboplatin (N=524)
System Organ Class | Adverse Reaction | Grade 1-4 Toxicity (%) | Grade 3-4 Toxicity (%) | Grades 1-4 Toxicity (%) | Grade 3-4 Toxicity (%)
Nervous system disorders | Peripheral neuropathya | 48 | 3 | 64 | 12
General disorders and administration site conditions | Edema peripheral | 10 | 0 | 4 | <1
Respiratory thoracic and mediastinal disorders | Epistaxis | 7 | 0 | 2 | 0
Musculoskeletal and connective tissue disorders | Arthralgia | 13 | <1 | 25 | 2
Musculoskeletal and connective tissue disorders | Myalgia | 10 | <1 | 19 | 2
a Peripheral neuropathy is defined by the MedDRA Version 14.0 SMQ neuropathy (broad scope).

For the ABRAXANE plus carboplatin treated group, 17/514 (3%) patients developed Grade 3 peripheral neuropathy and no patients developed Grade 4 peripheral neuropathy. Grade 3 neuropathy improved to Grade 1 or resolved in 10/17 patients (59%) following interruption or discontinuation of ABRAXANE.

Adenocarcinoma of the Pancreas

Adverse reactions were assessed in 421 patients who received ABRAXANE plus gemcitabine and 402 patients who received gemcitabine for the first-line systemic treatment of metastatic adenocarcinoma of the pancreas in a multicenter, multinational, randomized, controlled, open-label trial. Patients received a median treatment duration of 3.9 months in the ABRAXANE/gemcitabine group and 2.8 months in the gemcitabine group. For the treated population, the median relative dose intensity for gemcitabine was 75% in the ABRAXANE/gemcitabine group and 85% in the gemcitabine group. The median relative dose intensity of ABRAXANE was 81%.

Table 9 provides the frequency and severity of laboratory-detected abnormalities which occurred at a higher incidence for Grades 1-4 (≥ 5%) or for Grade 3-4 (≥ 2%) toxicity in ABRAXANE plus gemcitabine-treated patients.

Table 9: Selected Hematologic Laboratory-Detected Abnormalities with a Higher Incidence (≥ 5% for Grades 1-4 or ≥ 2% for Grades 3-4 Events) in the ABRAXANE/Gemcitabine Arm
 | ABRAXANE (125 mg/m^2)/ Gemcitabined |  | Gemcitabine
 | Grades 1-4 (%) | Grade 3-4 (%) | Grades 1-4 (%) | Grade 3-4 (%)
Neutropeniaa,b | 73 | 38 | 58 | 27
Thrombocytopeniab,c | 74 | 13 | 70 | 9
a 405 patients assessed in ABRAXANE/gemcitabine-treated group.
b 388 patients assessed in gemcitabine-treated group.
c 404 patients assessed in ABRAXANE/gemcitabine-treated group.
d Neutrophil growth factors were administered to 26% of patients in the ABRAXANE/gemcitabine group.

Table 10 provides the frequency and severity of adverse reactions which occurred with a difference of ≥ 5% for all grades or ≥ 2% for Grade 3 or higher in the ABRAXANE plus gemcitabine-treated group compared to the gemcitabine group.

Table 10: Selected Adverse Reactions with a Higher Incidence (≥5% for All Grade Toxicity or ≥2% for Grade 3 or Higher Toxicity) in the ABRAXANE/Gemcitabine Arm
System Organ Class | Adverse Reaction | ABRAXANE (125 mg/m^2) and gemcitabine (N=421) |  | Gemcitabine (N=402)
System Organ Class | Adverse Reaction | All Grades | Grade 3 or Higher | All Grades | Grade 3 or Higher
General disorders and administration site conditions | Fatigue | 248 (59%) | 77 (18%) | 183 (46%) | 37 (9%)
General disorders and administration site conditions | Peripheral edema | 194 (46%) | 13 (3%) | 122 (30%) | 12 (3%)
 | Pyrexia | 171 (41%) | 12 (3%) | 114 (28%) | 4 (1%)
 | Asthenia | 79 (19%) | 29 (7%) | 54 (13%) | 17 (4%)
 | Mucositis | 42 (10%) | 6 (1%) | 16 (4%) | 1 (<1%)
Gastrointestinal disorders | Nausea | 228 (54%) | 27 (6%) | 192 (48%) | 14 (3%)
 | Diarrhea | 184 (44%) | 26 (6%) | 95 (24%) | 6 (1%)
 | Vomiting | 151 (36%) | 25 (6%) | 113 (28%) | 15 (4%)
Skin and subcutaneous tissue disorders | Alopecia | 212 (50%) | 6 (1%) | 21 (5%) | 0
Skin and subcutaneous tissue disorders | Rash | 128 (30%) | 8 (2%) | 45 (11%) | 2 (<1%)
Nervous system disorders | Peripheral neuropathya | 227 (54%) | 70 (17%) | 51 (13%) | 3 (1%)
 | Dysgeusia | 68 (16%) | 0 | 33 (8%) | 0
 | Headache | 60 (14%) | 1 (<1%) | 38 (9%) | 1 (<1%)
Metabolism and nutrition disorders | Decreased appetite | 152 (36%) | 23 (5%) | 104 (26%) | 8 (2%)
Metabolism and nutrition disorders | Dehydration | 87 (21%) | 31 (7%) | 45 (11%) | 10 (2%)
 | Hypokalemia | 52 (12%) | 18 (4%) | 28 (7%) | 6 (1%)
Respiratory, thoracic and mediastinal disorders | Cough | 72 (17%) | 0 | 30 (7%) | 0
Respiratory, thoracic and mediastinal disorders | Epistaxis | 64 (15%) | 1 (<1%) | 14 (3%) | 1 (<1%)
Infections and infestations | Urinary tract infections b | 47 (11%) | 10 (2%) | 20 (5%) | 1 (<1%)
Musculoskeletal and connective tissue disorders | Pain in extremity | 48 (11%) | 3 (1%) | 24 (6%) | 3 (1%)
Musculoskeletal and connective tissue disorders | Arthralgia | 47 (11%) | 3 (1%) | 13 (3%) | 1 (<1%)
 | Myalgia | 44 (10%) | 4 (1%) | 15 (4%) | 0
Psychiatric disorders | Depression | 51 (12%) | 1 (<1%) | 24 (6%) | 0
a Peripheral neuropathy is defined by the MedDRA Version 15.0 Standard MedDRA Query neuropathy (broad scope).
b Urinary tract infections includes the preferred terms of: urinary tract infection, cystitis, urosepsis, urinary tract infection bacterial, and urinary tract infection enterococcal.

Additional clinically relevant adverse reactions that were reported in < 10% of the patients with adenocarcinoma of the pancreas who received ABRAXANE/gemcitabine included:

Infections & infestations: oral candidiasis, pneumonia
Vascular disorders: hypertension
Cardiac disorders: tachycardia, congestive cardiac failure
Eye disorders: cystoid macular edema

Peripheral Neuropathy
Grade 3 peripheral neuropathy occurred in 17% of patients who received ABRAXANE/gemcitabine compared to 1% of patients who received gemcitabine only; no patients developed Grade 4 peripheral neuropathy. The median time to first occurrence of Grade 3 peripheral neuropathy in the ABRAXANE arm was 140 days. Upon suspension of ABRAXANE dosing, the median time to improvement from Grade 3 peripheral neuropathy to ≤ Grade 1 was 29 days. Of ABRAXANE-treated patients with Grade 3 peripheral neuropathy, 44% resumed ABRAXANE at a reduced dose.

Sepsis
Sepsis occurred in 5% of patients who received ABRAXANE/gemcitabine compared to 2% of patients who received gemcitabine alone. Sepsis occurred both in patients with and without neutropenia. Risk factors for sepsis included biliary obstruction or presence of biliary stent.

Pneumonitis
Pneumonitis occurred in 4% of patients who received ABRAXANE/gemcitabine compared to 1% of patients who received gemcitabine alone. Two of 17 patients in the ABRAXANE arm with pneumonitis died.

6.2 Postmarketing Experience

The following adverse reactions have been identified during postapproval use of ABRAXANE or with paclitaxel injection and may be expected to occur with ABRAXANE. Because these reactions are reported voluntarily from a population of uncertain size, it is not always possible to reliably estimate their frequency or establish a causal relationship to drug exposure.

Hypersensitivity Reactions

Severe and sometimes fatal hypersensitivity reactions. Cross-hypersensitivity between ABRAXANE and other taxanes has been reported.

Cardiovascular

Congestive heart failure, left ventricular dysfunction, and atrioventricular block. Most patients were previously exposed to cardiotoxic drugs, such as anthracyclines, or had underlying cardiac history.

Respiratory

Pneumonitis, interstitial pneumonia, and pulmonary embolism

Radiation pneumonitis in patients receiving concurrent radiotherapy.

Lung fibrosis has been reported with paclitaxel injection.

Neurologic

Cranial nerve palsies and vocal cord paresis, as well as autonomic neuropathy resulting in paralytic ileus.

Vision Disorders

Reduced visual acuity due to cystoid macular edema (CME). After cessation of treatment, CME may improve, and visual acuity may return to baseline. Abnormal visual evoked potentials in patients treated with paclitaxel injection suggest persistent optic nerve damage.

Hepatic

Hepatic necrosis and hepatic encephalopathy leading to death in patients treated with paclitaxel injection.

Gastrointestinal (GI)

Intestinal obstruction, intestinal perforation, pancreatitis, and ischemic colitis. In patients treated with paclitaxel injection, neutropenic enterocolitis (typhlitis) despite the coadministration of G-CSF, alone and in combination with other chemotherapeutic agents.

Injection Site Reaction

Extravasation. Closely monitor the ABRAXANE infusion site for possible infiltration during drug administration [see Dosage and Administration 2.1)].

Severe events such as phlebitis, cellulitis, induration, necrosis, and fibrosis have been reported with paclitaxel injection. In some cases, the onset of the injection site reaction occurred during a prolonged infusion or was delayed up to ten days. Recurrence of skin reactions at a site of previous extravasation following administration of paclitaxel injection at a different site has been reported.

Metabolic and Nutritional Disorders

Tumor lysis syndrome

Other Clinical Events

Skin reactions including generalized or maculopapular rash, erythema, and pruritus.

Photosensitivity reactions, radiation recall phenomenon, scleroderma, and in some patients previously exposed to capecitabine, reports of palmar-plantar erythrodysesthesia. Stevens-Johnson syndrome and toxic epidermal necrolysis have been reported.

Conjunctivitis, cellulitis, and increased lacrimation have been reported with paclitaxel injection.

Accidental Exposure

Upon inhalation of paclitaxel, dyspnea, chest pain, burning eyes, sore throat, and nausea have been reported.

Following topical exposure, tingling, burning, and redness have been reported.

7 DRUG INTERACTIONS

The metabolism of paclitaxel is catalyzed by CYP2C8 and CYP3A4. Caution should be exercised when administering ABRAXANE concomitantly with medicines known to inhibit or induce either CYP2C8 or CYP3A4.

8 USE IN SPECIFIC POPULATIONS

8.1 Pregnancy

Risk Summary

Based on its mechanism of action and findings in animals, ABRAXANE can cause fetal harm when administered to a pregnant woman [see Clinical Pharmacology (12.1)]. There are no available human data on ABRAXANE use in pregnant women to inform the drug-associated risk.

In animal reproduction studies, administration of paclitaxel formulated as albumin-bound particles to pregnant rats during the period of organogenesis resulted in embryo-fetal toxicity at doses approximately 2% of the daily maximum recommended human dose on a mg/m^2 basis (see Data). Advise females of reproductive potential of the potential risk to a fetus.

The background rate of major birth defects and miscarriage is unknown for the indicated population. In the U.S. general population, the estimated background risk of major birth defects and miscarriage in clinically recognized pregnancies is 2% to 4% and 15% to 20%, respectively.

Data

Animal Data

In embryo-fetal development studies, intravenous administration of paclitaxel formulated as albumin-bound particles to rats during pregnancy, on gestation days 7 to 17 at doses of 6 mg/m^2 (approximately 2% of the daily maximum recommended human dose on a mg/m^2 basis) caused embryo-fetal toxicities, as indicated by intrauterine mortality, increased resorptions (up to 5-fold), reduced numbers of litters and live fetuses, reduction in fetal body weight, and increase in fetal anomalies. Fetal anomalies included soft tissue and skeletal malformations, such as eye bulge, folded retina, microphthalmia, and dilation of brain ventricles.

8.2 Lactation

Risk Summary

There are no data on the presence of paclitaxel in human milk, or its effect on the breastfed child or on milk production. In animal studies, paclitaxel and/or its metabolites were excreted into the milk of lactating rats (see Data). Because of the potential for serious adverse reactions in a breastfed child from ABRAXANE, advise lactating women not to breastfeed during treatment with ABRAXANE and for two weeks after the last dose.

Data

Animal Data

Following intravenous administration of radiolabeled paclitaxel to rats on days 9 to 10 postpartum, concentrations of radioactivity in milk were higher than in plasma and declined in parallel with the plasma concentrations.

8.3 Females and Males of Reproductive Potential

Based on animal studies and mechanism of action, ABRAXANE can cause fetal harm when administered to a pregnant woman [see Use in Specific Populations (8.1)].

Pregnancy Testing

Verify the pregnancy status of females of reproductive potential prior to starting treatment with ABRAXANE.

Contraception

Females

Advise females of reproductive potential to use effective contraception and avoid becoming pregnant during treatment with ABRAXANE and for at least six months after the last dose of ABRAXANE.

Males

Based on findings in genetic toxicity and animal reproduction studies, advise males with female partners of reproductive potential to use effective contraception and avoid fathering a child during treatment with ABRAXANE and for at least three months after the last dose of ABRAXANE [see Use in Specific Populations (8.1) and Nonclinical Toxicology (13.1)].

Infertility

Females and Males

Based on findings in animals, ABRAXANE may impair fertility in females and males of reproductive potential [see Nonclinical Toxicology (13.1)].

8.4 Pediatric Use

Safety and effectiveness in pediatric patients have not been established. Pharmacokinetics, safety, and antitumor activity of ABRAXANE were assessed in an open-label, dose escalation, dose expansion study (NCT01962103) in 96 pediatric patients aged 1.4 to < 17 years with recurrent or refractory pediatric solid tumors. The maximum tolerated dose (MTD) normalized for body surface area (BSA) was lower in pediatric patients compared to adults. No new safety signals were observed in pediatric patients across these studies.

Paclitaxel protein-bound exposures normalized by dose were higher in 96 pediatric patients (aged 1.4 to < 17 years) as compared to those in adults.

8.5 Geriatric Use

Of the 229 patients in the randomized study who received ABRAXANE for the treatment of metastatic breast cancer, 13% were at least 65 years of age and < 2% were 75 years or older. This study of ABRAXANE did not include a sufficient number of patients with metastatic breast cancer who were 65 years and older to determine whether they respond differently from younger patients.

A subsequent pooled analysis was conducted in 981 patients receiving ABRAXANE monotherapy for metastatic breast cancer, of which 15% were 65 years of age or older and 2% were 75 years of age or older. A higher incidence of epistaxis, diarrhea, dehydration, fatigue, and peripheral edema was found in patients 65 years of age or older.

Of the 514 patients in the randomized study who received ABRAXANE and carboplatin for the first-line treatment of non-small cell lung cancer, 31% were 65 years or older and 3.5% were 75 years or older. Myelosuppression, peripheral neuropathy, and arthralgia were more frequent in patients 65 years or older compared to patients younger than 65 years old. No overall difference in effectiveness, as measured by response rates, was observed between patients 65 years or older compared to patients younger than 65 years old.

Of the 431 patients in the randomized study who received ABRAXANE and gemcitabine for the first-line treatment of pancreatic adenocarcinoma, 41% were 65 years or older and 10% were 75 years or older. No overall differences in effectiveness were observed between patients who were 65 years of age or older and younger patients. Diarrhea, decreased appetite, dehydration, and epistaxis were more frequent in patients 65 years or older compared with patients younger than 65 years old. Clinical studies of ABRAXANE did not include sufficient number of patients with pancreatic cancer who were 75 years and older to determine whether they respond differently from younger patients.

8.6 Renal Impairment

No adjustment of the starting ABRAXANE dose is required for patients with mild to moderate renal impairment (estimated creatinine clearance 30 to <90 mL/min) [see Clinical Pharmacology (12.3)]. There are insufficient data to permit dosage recommendations in patients with severe renal impairment or end stage renal disease (estimated creatinine clearance <30 mL/min).

8.7 Hepatic Impairment

No adjustment of the starting ABRAXANE dose is required for patients with mild hepatic impairment (total bilirubin > ULN and ≤ 1.5 x ULN and aspartate aminotransferase [AST] ≤ 10 x ULN). Reduce ABRAXANE starting dose in patients with moderate to severe hepatic impairment [see Dosage and Administration (2.5) and Clinical Pharmacology (12.3)]. ABRAXANE is not recommended for use in patients with total bilirubin > 5 x ULN or AST > 10 x ULN [see Dosage and Administration (2.5), Warnings and Precautions (5.6), and Clinical Pharmacology (12.3)]. ABRAXANE is not recommended for use in patients with metastatic adenocarcinoma of the pancreas who have moderate to severe hepatic impairment [see Dosage and Administration (2.5)].

10 OVERDOSAGE

There is no known antidote for ABRAXANE overdosage. The primary anticipated complications of overdosage would consist of bone marrow suppression, sensory neurotoxicity, and mucositis.

11 DESCRIPTION

ABRAXANE for Injectable Suspension (paclitaxel protein-bound particles for injectable suspension) (albumin-bound) is paclitaxel formulated as albumin-bound nanoparticles with a mean particle size of approximately 130 nanometers. Paclitaxel exists in the particles in a non-crystalline, amorphous state. Paclitaxel is a microtubule inhibitor. The chemical name for paclitaxel is 5β,20-Epoxy-1,2α,4,7β,10β,13α-hexahydroxytax-11-en-9-one 4,10-diacetate 2-benzoate 13-ester with (2R,3S)-N-benzoyl-3-phenylisoserine. The empirical formula is C47H51NO14 and the molecular weight is 853.91. Paclitaxel has the following structural formula:

Paclitaxel is a white to off-white crystalline powder. It is highly lipophilic, insoluble in water, and melts at approximately 216°C to 217°C.

ABRAXANE is supplied as a white to yellow, sterile, lyophilized powder for reconstitution with 20 mL of 0.9% Sodium Chloride Injection, USP prior to intravenous infusion. Each single‑dose vial contains 100 mg of paclitaxel (bound to human albumin) and approximately 900 mg of human albumin (containing sodium caprylate and sodium acetyltryptophanate). Each milliliter (mL) of reconstituted suspension contains 5 mg paclitaxel formulated as albumin‑bound particles. ABRAXANE is free of solvents.

12 CLINICAL PHARMACOLOGY

12.1 Mechanism of Action

ABRAXANE is a microtubule inhibitor that promotes the assembly of microtubules from tubulin dimers and stabilizes microtubules by preventing depolymerization. This stability results in the inhibition of the normal dynamic reorganization of the microtubule network that is essential for vital interphase and mitotic cellular functions. Paclitaxel induces abnormal arrays or "bundles" of microtubules throughout the cell cycle and multiple asters of microtubules during mitosis.

12.3 Pharmacokinetics

The pharmacokinetics of total paclitaxel following 30- and 180-minute infusions of ABRAXANE at dose levels of 80 to 375 mg/m^2 (0.31 to 1.15 times the maximum approved recommended dosage) were determined in clinical studies. Dose levels of mg/m^2 refer to mg of paclitaxel in ABRAXANE. Following intravenous administration of ABRAXANE to patients with solid tumors, paclitaxel plasma concentrations declined in a biphasic manner, the initial rapid decline representing distribution to the peripheral compartment and the slower second phase representing drug elimination.

Following ABRAXANE infusion, paclitaxel exhibited linear drug exposure (AUC) across clinical doses ranging from 80 to 300 mg/m^2 (0.31 to 1.15 times the maximum approved recommended dosage). The pharmacokinetics of paclitaxel in ABRAXANE were independent of the duration of intravenous administration.

The pharmacokinetic data of 260 mg/m^2 ABRAXANE administered over a 30-minute infusion was compared to the pharmacokinetics of 175 mg/m^2 paclitaxel injection over a 3-hour infusion. Clearance was larger (43%) and the volume of distribution was higher (53%) for ABRAXANE than for paclitaxel injection. There were no differences in terminal half-lives.

Distribution
Following ABRAXANE administration to patients with solid tumors, paclitaxel is evenly distributed into blood cells and plasma and is highly bound to plasma proteins (94%). The total volume of distribution is approximately 1741 L; the large volume of distribution indicates extensive extravascular distribution and/or tissue binding of paclitaxel.

In a within-patient comparison study, the fraction of unbound paclitaxel in plasma was significantly higher with ABRAXANE (6.2%) than with solvent-based paclitaxel (2.3%). This contributes to significantly higher exposure to unbound paclitaxel with ABRAXANE compared with solvent-based paclitaxel, when the total exposure is comparable. In vitro studies of binding to human serum proteins, using paclitaxel concentrations ranging from 0.1 to 50 µg/mL, indicated that the presence of cimetidine, ranitidine, dexamethasone, or diphenhydramine did not affect protein binding of paclitaxel.

Elimination
At the clinical dose range of 80 to 300 mg/m^2 (0.31 to 1.15 times the maximum approved recommended dosage), the mean total clearance of paclitaxel ranges from 13 to 30 L/h/m^2 and the mean terminal half-life ranges from 13 to 27 hours.

Metabolism
In vitro studies with human liver microsomes and tissue slices showed that paclitaxel in ABRAXANE was metabolized primarily to 6α-hydroxypaclitaxel by CYP2C8; and to two minor metabolites, 3'-p-hydroxypaclitaxel and 6α, 3'-p-dihydroxypaclitaxel, by CYP3A4. In vitro, the metabolism of paclitaxel to 6α-hydroxypaclitaxel was inhibited by a number of agents (ketoconazole, verapamil, diazepam, quinidine, dexamethasone, cyclosporin, teniposide, etoposide, and vincristine), but the concentrations used exceeded those found in vivo following normal therapeutic doses. Testosterone, 17α-ethinyl estradiol, retinoic acid, and quercetin, a specific inhibitor of CYP2C8, also inhibited the formation of 6α-hydroxypaclitaxel in vitro. The pharmacokinetics of paclitaxel may also be altered in vivo as a result of interactions with compounds that are substrates, inducers, or inhibitors of CYP2C8 and/or CYP3A4 [see Drug Interactions (7)].

Excretion
After a 30-minute infusion of 260 mg/m^2 doses of ABRAXANE, the mean values for cumulative urinary recovery of unchanged drug (4%) indicated extensive non-renal clearance. Less than 1% of the total administered dose was excreted in urine as the metabolites 6α-hydroxypaclitaxel and 3'-p-hydroxypaclitaxel. Fecal excretion was approximately 20% of the total dose administered.

Specific Populations

No clinically meaningful differences in the pharmacokinetics of paclitaxel in ABRAXANE were observed based on body weight (40 to 143 kg), body surface area (1.3 to 2.4 m^2), sex, race (Asian vs. White), age (24 to 85 years), type of solid tumors, mild to moderate renal impairment (creatinine clearance 30 to <90 mL/min), and mild hepatic impairment (total bilirubin >1 to ≤1.5 x ULN and AST ≤10 x ULN).

Patients with moderate (total bilirubin >1.5 to 3 x ULN and AST ≤10 x ULN) or severe (total bilirubin >3 to 5 x ULN) hepatic impairment had a 22% to 26% decrease in the maximum elimination rate of paclitaxel and approximately 20% increase in mean paclitaxel AUC compared with patients with normal hepatic function (total bilirubin ≤ULN and AST ≤ULN) [see Dosage and Administration (2.5) and Use in Specific Populations (8.7)].

The effect of severe renal impairment or end stage renal disease (creatinine clearance < 30 mL/min) on the pharmacokinetics of paclitaxel in ABRAXANE is unknown.

Drug Interaction Studies
Carboplatin: Administration of carboplatin immediately after the completion of the ABRAXANE infusion to patients with NSCLC did not cause clinically meaningful changes in paclitaxel exposure. The observed mean AUCinf of free carboplatin was approximately 23% higher than the targeted value (6 min*mg/mL), but its mean half-life and clearance were consistent with those reported in the absence of paclitaxel.

13 NONCLINICAL TOXICOLOGY

13.1 Carcinogenesis, Mutagenesis, Impairment of Fertility

The carcinogenic potential of ABRAXANE has not been studied.

Paclitaxel was clastogenic in vitro (chromosome aberrations in human lymphocytes) and in vivo (micronucleus test in mice). Paclitaxel was not mutagenic in the Ames test or the CHO/HGPRT gene mutation assay.

Administration of paclitaxel formulated as albumin-bound particles to male rats at 42 mg/m^2 on a weekly basis (approximately 16% of the daily maximum recommended human exposure on a body surface area basis) for 11 weeks prior to mating with untreated female rats resulted in significantly reduced fertility accompanied by decreased pregnancy rates and increased loss of embryos in mated females. A dose of 42 mg/m^2 also reduced male reproductive organ weights, mating performance, and sperm production. Testicular atrophy/degeneration was observed in single-dose toxicology studies in animals administered paclitaxel formulated as albumin-bound particles at doses lower than the recommended human dose; doses were 54 mg/m^2 in rodents and 175 mg/m^2 in dogs. Similar testicular degeneration was seen in monkeys administered three weekly doses of 108 mg/m^2 paclitaxel formulated as albumin bound particles.

Administration of paclitaxel prior to and during mating produced impairment of fertility in male and female rats. Paclitaxel caused reduced fertility and reproductive indices, and increased embryo-fetal toxicity.

14 CLINICAL STUDIES

14.1 Metastatic Breast Cancer

Data from 106 patients accrued in two single arm open label studies and from 460 patients enrolled in a randomized comparative study were available to support the use of ABRAXANE in metastatic breast cancer.

Single Arm Open Label Studies
In one study, ABRAXANE was administered as a 30-minute infusion at a dose of 175 mg/m^2 to 43 patients with metastatic breast cancer. The second trial utilized a dose of 300 mg/m^2 as a 30-minute infusion in 63 patients with metastatic breast cancer. Cycles were administered at 3-week intervals. Objective responses were observed in both studies.

Randomized Comparative Study
This multicenter trial was conducted in 460 patients with metastatic breast cancer. Patients were randomized to receive ABRAXANE at a dose of 260 mg/m^2 given as a 30-minute infusion, or paclitaxel injection at 175 mg/m^2 given as a 3-hour infusion. Sixty-four percent of patients had impaired performance status (ECOG 1 or 2) at study entry; 79% had visceral metastases; and 76% had > 3 sites of metastases. Fourteen percent of the patients had not received prior chemotherapy; 27% had received chemotherapy in the adjuvant setting, 40% in the metastatic setting and 19% in both metastatic and adjuvant settings. Fifty-nine percent received study drug as second or greater than second-line therapy. Seventy-seven percent of the patients had been previously exposed to anthracyclines.

In this trial, patients in the ABRAXANE treatment arm had a statistically significantly higher reconciled target lesion response rate (the trial primary endpoint) of 21.5% (95% CI: 16.2% to 26.7%), compared to 11.1% (95% CI: 6.9% to 15.1%) for patients in the paclitaxel injection treatment arm. See Table 11. There was no statistically significant difference in overall survival between the two study arms.

Table 11: Efficacy Results from Randomized Metastatic Breast Cancer Trial
 |  | ABRAXANE 260 mg/m^2 | Paclitaxel Injection 175 mg/m^2
Reconciled Target Lesion Response Rate (primary endpoint)a
All randomized patients | Response Rate [95% CI] | 50/233 (21.5%) [16.19% – 26.73%] | 25/227 (11.1%) [6.94% – 15.09%]
All randomized patients | p-valueb | 0.003
Patients who had failed combination chemotherapy or relapsed within 6 months of adjuvant chemotherapyc | Response Rate [95% CI] | 20/129 (15.5%) [9.26% – 21.75%] | 12/143 (8.4%) [3.85% – 12.94%]
a Reconciled Target Lesion Response Rate (TLRR) was the prospectively defined protocol specific endpoint, based on independent radiologic assessment of tumor responses reconciled with investigator responses (which also included clinical information) for the first 6 cycles of therapy. The reconciled TLRR was lower than the investigator Reported Response Rates, which are based on all cycles of therapy.
b From Cochran-Mantel-Haenszel test stratified by 1st line vs. > 1st line therapy.
c Prior therapy included an anthracycline unless clinically contraindicated.

14.2 Non-Small Cell Lung Cancer

A multicenter, randomized, open-label study was conducted in 1052 chemotherapy naive patients with Stage IIIb/IV non-small cell lung cancer to compare ABRAXANE in combination with carboplatin to paclitaxel injection in combination with carboplatin as first-line treatment in patients with advanced non-small cell lung cancer. ABRAXANE was administered as an intravenous infusion over 30 minutes at a dose of 100 mg/m^2 on Days 1, 8, and 15 of each 21-day cycle. Paclitaxel injection was administered as an intravenous infusion over 3 hours at a dose of 200 mg/m^2, following premedication. In both treatment arms carboplatin at a dose of AUC = 6 mg•min/mL was administered intravenously on Day 1 of each 21-day cycle after completion of ABRAXANE/paclitaxel infusion. Treatment was administered until disease progression or development of an unacceptable toxicity. The major efficacy outcome measure was overall response rate as determined by a central independent review committee using RECIST guidelines (Version 1.0).

In the intent-to-treat (all-randomized) population, the median age was 60 years, 75% were men, 81% were White, 49% had adenocarcinoma, 43% had squamous cell lung cancer, 76% were ECOG PS 1, and 73% were current or former smokers. Patients received a median of 6 cycles of treatment in both study arms.

Patients in the ABRAXANE/carboplatin arm had a statistically significantly higher overall response rate compared to patients in the paclitaxel injection/carboplatin arm [(33% versus 25%) see Table 12]. There was no statistically significant difference in overall survival between the two study arms.

Table 12: Efficacy Results from Randomized Non-Small Cell Lung Cancer Trial (Intent-to-Treat Population)
 | ABRAXANE (100 mg/m^2 weekly) + carboplatin (N=521) | Paclitaxel Injection (200 mg/m^2 every 3 weeks) + carboplatin (N=531)
Overall Response Rate (ORR)
Confirmed complete or partial overall response, n (%) | 170 (33%) | 132 (25%)
95% CI | 28.6, 36.7 | 21.2, 28.5
P-value (Chi-Square test) | 0.005
Median DoR in months (95% CI) | 6.9 (5.6, 8.0) | 6.0 (5.6, 7.1)
Overall Response Rate by Histology
Carcinoma/Adenocarcinoma | 66/254 (26%) | 71/264 (27%)
Squamous Cell Carcinoma | 94/229 (41%) | 54/221 (24%)
Large Cell Carcinoma | 3/9 (33%) | 2/13 (15%)
Other | 7/29 (24%) | 5/33 (15%)
CI = confidence interval; DoR= Duration of response.

14.3 Adenocarcinoma of the Pancreas

A multicenter, multinational, randomized, open-label study was conducted in 861 patients comparing ABRAXANE plus gemcitabine versus gemcitabine monotherapy as first-line treatment of metastatic adenocarcinoma of the pancreas. Key eligibility criteria were Karnofsky Performance Status (KPS) ≥70, normal bilirubin level, transaminase levels ≤ 2.5 times the upper limit of normal (ULN) or ≤ 5 times the ULN for patients with liver metastasis, no prior cytotoxic chemotherapy in the adjuvant setting or for metastatic disease, no ongoing active infection requiring systemic therapy, and no history of interstitial lung disease. Patients with rapid decline in KPS (≥10%) or serum albumin (≥20%) during the 14 day screening period prior to study randomization were ineligible.

A total of 861 patients were randomized (1:1) to the ABRAXANE/gemcitabine arm (N=431) or to the gemcitabine arm (N=430).

Randomization was stratified by geographic region (Australia, Western Europe, Eastern Europe, or North America), KPS (70 to 80 versus 90 to 100), and presence of liver metastasis (yes versus no). Patients randomized to ABRAXANE/gemcitabine received ABRAXANE 125 mg/m^2 as an intravenous infusion over 30-40 minutes followed by gemcitabine 1000 mg/m^2 as an intravenous infusion over 30-40 minutes on Days 1, 8, and 15 of each 28-day cycle. Patients randomized to gemcitabine received 1000 mg/m^2 as an intravenous infusion over 30-40 minutes weekly for 7 weeks followed by a 1-week rest period in Cycle 1 then as 1000 mg/m^2 on Days 1, 8, and 15 of each subsequent 28-day cycle. Patients in both arms received treatment until disease progression or unacceptable toxicity. The major efficacy outcome measure was overall survival (OS). Additional outcome measures were progression-free survival (PFS) and overall response rate (ORR), both assessed by independent, central, blinded radiological review using RECIST (version 1.0).

In the intent-to-treat (all randomized) population, the median age was 63 years (range 27-88 years) with 42% ≥ 65 years of age; 58% were men; 93% were White and KPS was 90-100 in 60%. Disease characteristics included 46% of patients with 3 or more metastatic sites; 84% of patients had liver metastasis; and the location of the primary pancreatic lesion was in the head of pancreas (43%), body (31%), or tail (25%).

Results for overall survival, progression-free survival, and overall response rate are shown in Table 13.

Table 13: Efficacy Results from Randomized Study in Patients with Adenocarcinoma of the Pancreas (ITT Population)
 | ABRAXANE (125 mg/m^2) and gemcitabine (N = 431) | Gemcitabine (N = 430)
Overall Survival
Number of deaths, n (%) | 333 (77) | 359 (83)
Median Overall Survival (months) | 8.5 | 6.7
95% CI | 7.9, 9.5 | 6.0, 7.2
HR (95% CI) a | 0.72 (0.62, 0.83)
P-valueb | <0.0001
Progression-free Survivalc
Death or progression, n (%) | 277 (64) | 265 (62)
Median Progression-free Survival (months) | 5.5 | 3.7
95% CI | 4.5, 5.9 | 3.6, 4.0
HR (95% CI) a | 0.69 (0.58, 0.82)
P-valueb | <0.0001
Overall Response Ratec
Confirmed complete or partial overall response, n (%) | 99 (23) | 31 (7)
95% CI | 19.1, 27.2 | 5.0, 10.1
P-value d | <0.0001
CI = confidence interval, HR = hazard ratio of ABRAXANE plus gemcitabine / gemcitabine, ITT = intent-to-treat population.
a Stratified Cox proportional hazard model.
b Stratified log-rank test stratified by geographic region (North America versus Others), Karnofsky performance score (70 to 80 versus 90 to 100), and presence of liver metastasis (yes versus no).
c Based on Independent Radiological Reviewer Assessment.
d Chi-square test.

In exploratory analyses conducted in clinically relevant subgroups with a sufficient number of subjects, the treatment effects on overall survival were similar to that observed in the overall study population.

Figure 1: Kaplan-Meier Curve of Overall Survival (Intent-to-Treat Population)

15 REFERENCES

1. OSHA Hazardous Drugs. OSHA http://www.osha.gov/SLTC/hazardousdrugs/index.html

16 HOW SUPPLIED/STORAGE AND HANDLING

ABRAXANE for Injectable Suspension (paclitaxel protein-bound particles for injectable suspension) (albumin-bound) is a white to yellow, sterile lyophilized powder supplied as:

NDC : 68817-134-50 100 mg of paclitaxel in a single-dose vial, individually packaged in a carton.

STORAGE AND HANDLING

Store the vials in original cartons at 20°C to 25°C (68°F to 77°F). Retain in the original package to protect from bright light.

Abraxane is a cytotoxic drug. Follow applicable special handling and disposal procedures.^1

17 PATIENT COUNSELING INFORMATION

Advise the patient to read the approved patient labeling (Patient Information).

Severe Myelosuppression

- Patients must be informed of the risk of low blood cell counts and severe and life-threatening infections and instructed to contact their healthcare provider immediately for fever or evidence of infection [see Warnings and Precautions (5.1), (5.3)].

Severe Neuropathy

- Patients must be informed that sensory neuropathy occurs frequently with ABRAXANE and patients should advise their healthcare providers of numbness, tingling, pain, or weakness involving the extremities [see Warnings and Precautions (5.2)].

Pneumonitis

- Instruct patients to contact their healthcare provider immediately for sudden onset of dry persistent cough, or shortness of breath [see Warnings and Precautions (5.4)].

Severe Hypersensitivity

- Instruct patients to contact their healthcare provider for signs of an allergic reaction, which could be severe and sometimes fatal [see Warnings and Precautions (5.5)].

Common Adverse Reactions

- Explain to patients that alopecia, fatigue/asthenia, and myalgia/arthralgia occur frequently with ABRAXANE.
- Instruct patients to contact their healthcare providers for persistent vomiting, diarrhea, or signs of dehydration [see Adverse Reactions (6)].

Embryo-Fetal Toxicity

- ABRAXANE injection can cause fetal harm. Advise patients to avoid becoming pregnant while receiving this drug. Females of reproductive potential should use effective contraception during treatment with ABRAXANE and for at least six months after the last dose of ABRAXANE [see Warnings and Precautions (5.8) and Use in Specific Populations (8.1, 8.3)].
- Advise male patients with female partners of reproductive potential to use effective contraception and avoid fathering a child during treatment with ABRAXANE and for at least three months after the last dose of ABRAXANE [see Use in Specific Populations (8.3)].

Lactation

- Advise patients not to breastfeed while taking ABRAXANE and for two weeks after receiving the last dose [see Use in Specific Populations (8.2)].

Infertility

- Advise males and females of reproductive potential that ABRAXANE may impair fertility [see Use in Specific Populations (8.3)].

Marketed by: Bristol-Myers Squibb Company
Princeton, NJ 08543 USA

ABRAXANE® is a trademark of Abraxis BioScience, LLC, a Bristol-Myers Squibb company.

U.S. Patent Numbers: www.bms.com/patient-and-caregivers/our-medicines.html

ABRPI.013/PPI.013

Patient Information
ABRAXANE® (ah-BRAKS-ane)
(paclitaxel protein-bound particles for injectable suspension)
(albumin-bound)

What is ABRAXANE?

ABRAXANE is a prescription medicine used to treat:

- advanced breast cancer in people who have already received certain other medicines for their cancer.
- advanced non-small cell lung cancer (NSCLC), in combination with carboplatin in people who cannot be treated with surgery or radiation.
- advanced pancreatic cancer, when used in combination with gemcitabine as the first medicine for advanced pancreatic cancer.

It is not known if ABRAXANE is safe or effective in children.

Do not receive ABRAXANE if:

- your white blood cell count is below 1,500 cells/ mm^3.
- you have had a severe allergic reaction to ABRAXANE.

Before you receive ABRAXANE, tell your healthcare provider about all of your medical conditions, including if you:

- have liver or kidney problems.
- had a prior allergic reaction to a taxane.
- are pregnant or plan to become pregnant. ABRAXANE can harm your unborn baby.
  Females who are able to become pregnant:
  - Your healthcare provider will check to see if you are pregnant before you start treatment with ABRAXANE.
  - You should not become pregnant during your treatment and for at least six months after the last dose of ABRAXANE.
  - You should use effective birth control (contraception) during your treatment and for at least six months after the last dose of ABRAXANE. Talk to your healthcare provider about birth control methods you can use during this time.

Males with a female sexual partner who can become pregnant:
  - ABRAXANE can harm the unborn baby of your partner.
  - You should not father a child during your treatment and for at least three months after the last dose of ABRAXANE.
  - You should use effective birth control (contraception) during your treatment and for at least three months after the last dose of ABRAXANE.
- are breastfeeding or plan to breastfeed. Do not breastfeed during your treatment and for two weeks after the last dose of ABRAXANE.

Tell your healthcare provider about all the medicines you take, including prescription and over-the-counter medicines, vitamins, and herbal supplements.

Know the medicines you take. Keep a list to show your healthcare provider and pharmacist when you get a new medicine.

How will I receive ABRAXANE?

- Your healthcare provider will prescribe ABRAXANE in an amount that is right for you.
- Your healthcare provider may give you certain medicines to help prevent allergic reactions if you have had an allergic reaction to ABRAXANE in the past.
- ABRAXANE will be given to you by intravenous (IV) infusion into your vein.
- Your healthcare provider should do blood tests regularly during treatment with ABRAXANE.
- Your healthcare provider may stop your treatment, delay your treatment, or change your dose of ABRAXANE if you have certain side effects.

What are the possible side effects of ABRAXANE?

ABRAXANE may cause serious side effects, including:

- severe decreased blood cell counts. ABRAXANE can cause a severe decrease in neutrophils, a type of white blood cell which helps fight infections, and blood cells called platelets which help to clot blood. Your healthcare provider will check your blood cell count during your treatment with ABRAXANE.
- severe nerve problems (neuropathy). Tell your healthcare provider if you have numbness, tingling, pain, or weakness in your hands or feet.
- severe infection (sepsis). If you receive ABRAXANE in combination with gemcitabine, infections can be severe and lead to death. Tell your healthcare provider right away if you have a fever (temperature greater than 100.4° F) or develop signs of infection.
- lung or breathing problems. If you receive ABRAXANE in combination with gemcitabine, lung or breathing problems may be severe and can lead to death. Tell your healthcare provider right away if you suddenly get a dry cough that will not go away or shortness of breath.
- severe allergic reactions. Severe allergic reactions are medical emergencies that can happen in people who receive ABRAXANE and can lead to death. You may have an increased risk of having an allergic reaction to ABRAXANE if you are allergic to other taxane medicines. Your healthcare provider will monitor you closely for allergic reactions during your infusion of ABRAXANE. Tell your healthcare provider right away if you get any of these signs of a serious allergic reaction: trouble breathing, sudden swelling of your face, lips, tongue, throat, or trouble swallowing, hives (raised bumps), rash, or redness all over your body.

The most common side effects of ABRAXANE in people with breast cancer include:

- hair loss
- numbness, tingling, pain, or weakness in the hands or feet
- tiredness
- changes in your liver function tests
- nausea
- diarrhea
- infections

- decreased white blood cell count
- abnormal heartbeat
- joint and muscle pain
- low red blood cell count (anemia). Red blood cells carry oxygen to your body tissues. Tell your healthcare provider if you feel weak, tired, or short of breath.

The most common side effects of ABRAXANE in people with non-small cell lung cancer include:

- low red blood cell count (anemia)
- decreased platelet cell count
- numbness, tingling, pain, or weakness in the hands or feet
- tiredness

- decreased white blood cell count
- hair loss
- nausea

The most common side effects of ABRAXANE in people with pancreatic cancer include:

- decreased white blood cell count
- numbness, tingling, pain, or weakness in the hands or feet
- hair loss
- diarrhea
- vomiting
- rash

- tiredness
- nausea
- swelling in the hands or feet
- fever
- decreased appetite
- signs of dehydration including thirst, dry mouth, dark yellow urine, decreased urine, headache, or muscle cramps

Tell your healthcare provider if you have vomiting, diarrhea, or signs of dehydration that does not go away.

ABRAXANE may cause fertility problems in males and females, which may affect your ability to have a child. Talk to your healthcare provider if this is a concern for you. These are not all of the possible side effects of ABRAXANE.

Call your doctor for medical advice about side effects. You may report side effects to FDA at 1-800-FDA-1088.

General information about the safe and effective use of ABRAXANE.

Medicines are sometimes prescribed for purposes other than those listed in a Patient Information leaflet. You can ask your healthcare provider or pharmacist for information about ABRAXANE that is written for health professionals.

What are the ingredients in ABRAXANE?

Active ingredient: paclitaxel (bound to human albumin).

Other ingredient: human albumin (containing sodium caprylate and sodium acetyltryptophanate).

Marketed by: Bristol-Myers Squibb Company, Princeton, NJ 08543 USA

ABRAXANE® is a trademark of Abraxis BioScience, LLC, a Bristol-Myers Squibb company.

U.S. Patent Numbers: www.bms.com/patient-and-caregivers/our-medicines.html

ABRPPI.013

For more information, call 1-800-721-5072.

This Patient Information has been approved by the U.S. Food and Drug Administration.

Revised: 10/2022

PACKAGE LABEL

PRINCIPAL DISPLAY PANEL - 100 mg Vial

NDC 68817-134-50
103450

Abraxane®
for Injectable Suspension

(paclitaxel protein-bound particles for injectable suspension)
(albumin-bound)

100 mg per vial
Single Use Vial

Discard any unused portion.

For Intravenous Use Only
Rx only

Functional properties differ from other
paclitaxel products. DO NOT SUBSTITUTE.

PACKAGE LABEL

PRINCIPAL DISPLAY PANEL - 100 mg Vial Carton

NDC 68817-134-50
103450

Abraxane®
for Injectable Suspension

(paclitaxel protein-bound particles for injectable suspension)
(albumin-bound)

100 mg per vial
Single Use Vial

Discard any unused portion.

For Intravenous Use Only
Rx only

Functional properties differ from other
paclitaxel products. DO NOT SUBSTITUTE.